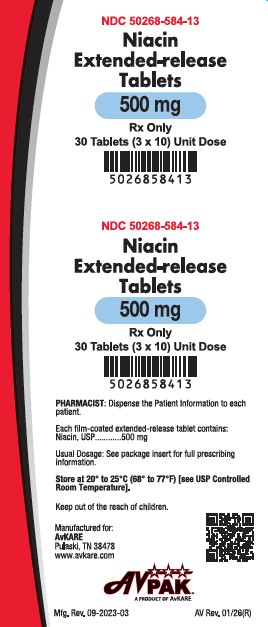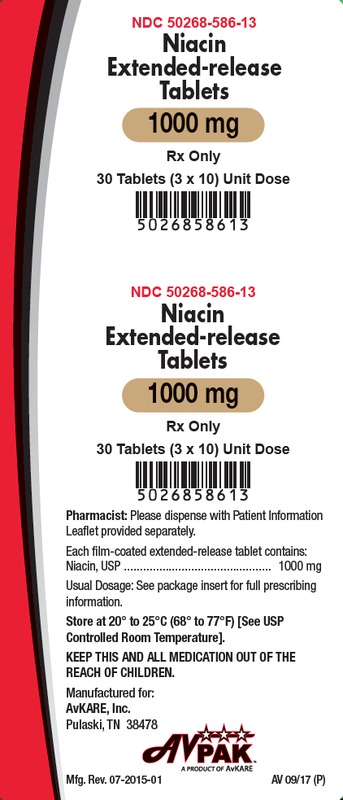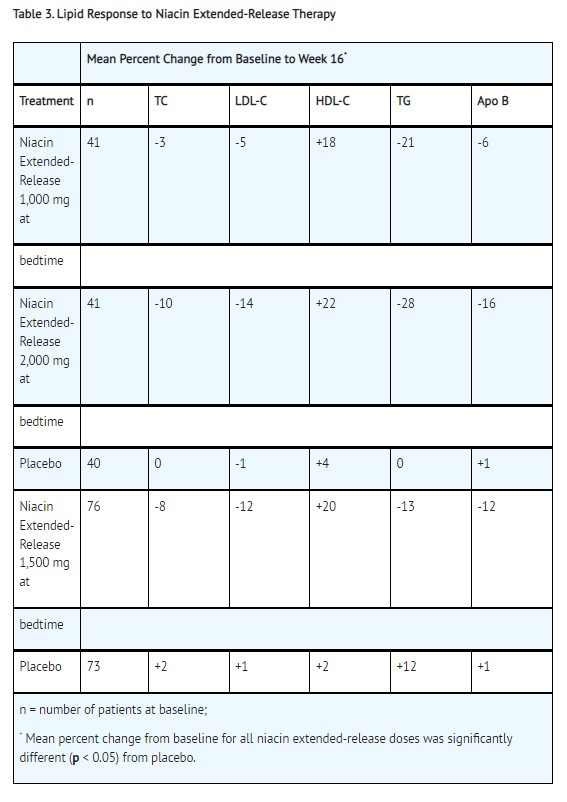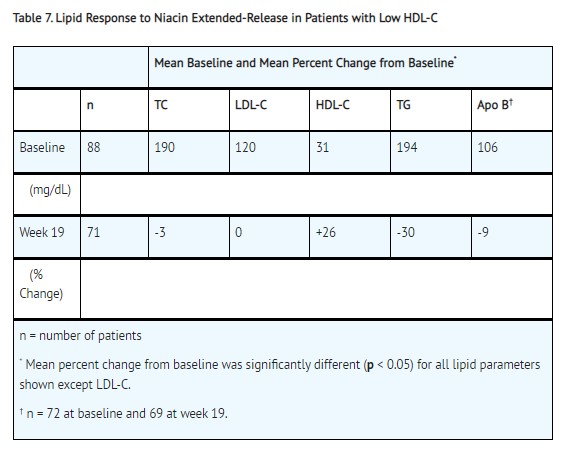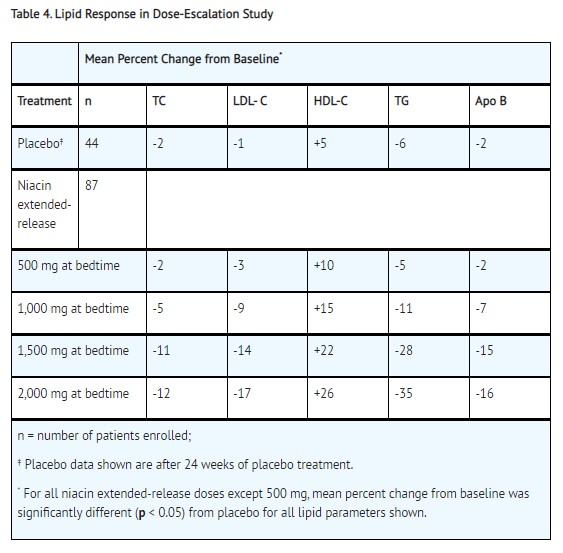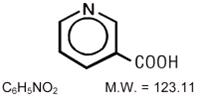 DRUG LABEL: Niacin
NDC: 50268-586 | Form: TABLET, EXTENDED RELEASE
Manufacturer: AvPAK
Category: prescription | Type: HUMAN PRESCRIPTION DRUG LABEL
Date: 20260225

ACTIVE INGREDIENTS: NIACIN 1000 mg/1 1
INACTIVE INGREDIENTS: FD&C YELLOW NO. 6; HYDROXYETHYL CELLULOSE (4000 MPA.S AT 1%); HYPROMELLOSES; FERRIC OXIDE RED; FERRIC OXIDE YELLOW; POLYETHYLENE GLYCOL 400; STEARIC ACID; TITANIUM DIOXIDE

HIGHLIGHTS OF PRESCRIBING INFORMATION

Niacin Extended-Release Tablets
These highlights do not include all the information needed to use niacin extended-release tablets safely and effectively. See full prescribing information for niacin extended-release tablets.
NIACIN extended-release tablets, film-coated, for oral use.
Initial U.S. Approval: 1997

RECENT MAJOR CHANGES

Indications and Usage, Combination With a Statin – removal 04/2015

Dosage and Administration, Combination With a Statin – removal (2) 04/2015

INDICATIONS AND USAGE

Niacin extended-release tablets contain extended-release niacin (nicotinic acid), and are indicated:

- To reduce elevated TC, LDL-C, Apo B and TG, and to increase HDL-C in patients with primary hyperlipidemia and mixed dyslipidemia. (1)
- To reduce the risk of recurrent nonfatal myocardial infarction in patients with a history of myocardial infarction and hyperlipidemia. (1)
- In combination with a bile acid binding resin:
- Slows progression or promotes regression of atherosclerotic disease in patients with a history of coronary artery disease (CAD) and hyperlipidemia. (1)
- As an adjunct to diet to reduce elevated TC and LDL-C in adult patients with primary hyperlipidemia. (1)
- To reduce TG in adult patients with severe hypertriglyceridemia. (1)

Limitations of use:

Addition of niacin extended-release tablets did not reduce cardiovascular morbidity or mortality among patients treated with simvastatin in a large, randomized controlled trial (5.1).

2 DOSAGE AND ADMINISTRATION

- Niacin extended-release tablets should be taken at bedtime with a low-fat snack. (2)
- Dose range: 500 mg to 2000 mg once daily. (2)
- Therapy with niacin extended-release tablets must be initiated at 500 mg at bedtime in order to reduce the incidence and severity of side effects which may occur during early therapy and should not be increased by more than 500 mg in any four week period. (2)
- Maintenance dose: 1000 to 2000 mg once daily. (2)
- Doses greater than 2000 mg daily are not recommended. (2)

3 DOSAGE FORMS AND STRENGTHS

Unscored film-coated tablets for oral administration: 500 mg and 1000 mg niacin extended-release. (3)

4 CONTRAINDICATIONS

- Active liver disease, which may include unexplained persistent elevations in hepatic transaminase levels. (4, 5.3)
- Active peptic ulcer disease. (4)
- Arterial bleeding. (4)
- Known hypersensitivity to product components. (4, 6.1)

5 WARNINGS AND PRECAUTIONS

- Severe hepatic toxicity has occurred in patients substituting sustained-release niacin for immediate-release niacin at equivalent doses. (5.3)
- Myopathy has been reported in patients taking niacin extended-release. The risk for myopathy and rhabdomyolysis are increased among elderly patients; patients with diabetes, renal failure, or uncontrolled hypothyroidism; and patients being treated with a statin. (5.2)
- Liver enzyme abnormalities and monitoring: Persistent elevations in hepatic transaminase can occur. Monitor liver enzymes before and during treatment. (5.3)
- Use with caution in patients with unstable angina or in the acute phase of an MI. (5)
- Niacin extended-release can increase serum glucose levels. Glucose levels should be closely monitored in diabetic or potentially diabetic patients particularly during the first few months of use or dose adjustment. (5.4)

6 ADVERSE REACTIONS

Most common adverse reactions (incidence >5% and greater than placebo) are flushing, diarrhea, nausea, vomiting, increased cough, and pruritus. (6.1)

Flushing of the skin may be reduced in frequency or severity by pretreatment with aspirin (up to the recommended dose of 325 mg taken 30 minutes prior to niacin extended-release dose). (2.2)

To report SUSPECTED ADVERSE REACTIONS, contact AvKARE at 1-855-361-3993 or www.avkare.com or FDA at 1-800-FDA-1088 or www.fda.gov/medwatch.

7 DRUG INTERACTIONS

- Statins: Caution should be used when prescribing niacin with statins as these agents can increase risk of myopathy/rhabdomyolysis. (5.2, 7.1)
- Bile Acid Sequestrants: Bile acid sequestrants have a high niacin-binding capacity and should be taken at least 4 to 6 hours before niacin extended-release administration. (7.2)

8 USE IN SPECIFIC POPULATIONS

- Pregnancy: Discontinue in patients with hyperlipidemia; assess individual risks and benefits in patients with hypertriglyceridemia. (8.1)
- Lactation: Advise patients not to breastfeed during treatment. (8.2)
- Renal impairment: Niacin extended- release should be used with caution in patients with renal impairment. (5, 8.6)
- Hepatic impairment: Niacin extended-release is contraindicated in active liver disease or significant or unexplained hepatic dysfunction or unexplained elevations of serum transaminases. (4, 5, 5.3, 8.7)

FULL PRESCRIBING INFORMATION

INDICATIONS AND USAGE

Therapy with lipid-altering agents should be only one component of multiple risk factor intervention in individuals at significantly increased risk for atherosclerotic vascular disease due to hyperlipidemia. Niacin therapy is indicated as an adjunct to diet when the response to a diet restricted in saturated fat and cholesterol and other nonpharmacologic measures alone has been inadequate.

1. Niacin extended-release tablets are indicated to reduce elevated TC, LDL-C, Apo B and TG levels, and to increase HDL-C in patients with primary hyperlipidemia and mixed dyslipidemia.
2. In patients with a history of myocardial infarction and hyperlipidemia, niacin is indicated to reduce the risk of recurrent nonfatal myocardial infarction.
3. In patients with a history of coronary artery disease (CAD) and hyperlipidemia, niacin, in combination with a bile acid binding resin, is indicated to slow progression or promote regression of atherosclerotic disease.
4. Niacin extended-release tablets in combination with a bile acid binding resin is indicated to reduce elevated TC and LDL-C levels in adult patients with primary hyperlipidemia.
5. Niacin is also indicated as adjunctive therapy for treatment of adult patients with severe hypertriglyceridemia who present a risk of pancreatitis and who do not respond adequately to a determined dietary effort to control them.

Limitations of Use

Addition of niacin extended-release tablets did not reduce cardiovascular morbidity or mortality among patients treated with simvastatin in a large, randomized controlled trial (AIM-HIGH) [see Warnings and Precautions (5.1)] .

2 DOSAGE AND ADMINISTRATION

2.1 Initial Dosing

Niacin extended-release tablets should be taken at bedtime, after a low-fat snack, and doses should be individualized according to patient response. Therapy with niacin extended-release tablets must be initiated at 500 mg at bedtime in order to reduce the incidence and severity of side effects which may occur during early therapy. The recommended dose escalation is shown in Table 1 below.

Table 1. Recommended Dosing

 | Week(s) | Daily dose | Niacin Extended-Release Tablets Dosage
INITIAL; TITRATION | 1 to 4 | 500 mg | 1 Niacin Extended-Release Tablet 500 mg at bedtime
SCHEDULE | 5 to 8 | 1000 mg | 1 Niacin Extended-Release Tablet 1000 mg or; 2 Niacin Extended-Release Tablets 500 mg at bedtime
 | * | 1500 mg | 3 Niacin Extended-Release Tablets 500 mg at bedtime
 | * | 2000 mg | 2 Niacin Extended-Release Tablets 1000 mg or; 4 Niacin Extended-Release Tablets 500 mg at bedtime
* After Week 8, titrate to patient response and tolerance. If response to 1000 mg daily is inadequate, increase dose to 1500 mg daily; may subsequently increase dose to 2000 mg daily. Daily dose should not be increased more than 500 mg in a 4-week period, and doses above 2000 mg daily are not recommended. Women may respond at lower doses than men.

2.2 Maintenance Dose

The daily dosage of niacin extended-release tablets should not be increased by more than 500 mg in any 4–week period. The recommended maintenance dose is 1000 mg (two 500 mg tablets or one 1000 mg tablet) to 2000 mg (two 1000 mg tablets or four 500 mg tablets) once daily at bedtime. Doses greater than 2000 mg daily are not recommended. Women may respond at lower niacin extended-release tablets doses than men [see Clinical Studies (14.2)] .

Single-dose bioavailability studies have demonstrated that two of the 500 mg and one of the 1000 mg tablet strengths are interchangeable but three of the 500 mg and two of the 750 mg tablet strengths are not interchangeable.

Tolerance to flushing develops rapidly over the course of several weeks. Flushing, pruritus, and gastrointestinal distress are also greatly reduced by slowly increasing the dose of niacin and avoiding administration on an empty stomach. Concomitant alcoholic, hot drinks or spicy foods may increase the side effects of flushing and pruritus and should be avoided around the time of niacin extended-release tablets ingestion.

Equivalent doses of niacin extended-release tablets should not be substituted for sustained-release (modified-release, timed-release) niacin preparations or immediate-release (crystalline) niacin [see Warnings and Precautions (5)] . Patients previously receiving other niacin products should be started with the recommended niacin extended-release tablets titration schedule (see Table 1), and the dose should subsequently be individualized based on patient response.

If niacin extended-release tablets therapy is discontinued for an extended period, reinstitution of therapy should include a titration phase (see Table 1).

Niacin extended-release tablets should be taken whole and should not be broken, crushed or chewed before swallowing.

2.3 Dosage in Patients with Renal or Hepatic Impairment

Use of niacin extended-release tablets in patients with renal or hepatic impairment has not been studied. Niacin extended-release tablets are contraindicated in patients with significant or unexplained hepatic dysfunction. Niacin extended-release tablets should be used with caution in patients with renal impairment [see Warnings and Precautions (5)] .

3 DOSAGE FORMS AND STRENGTHS

- 500 mg light orange to orange colored, round shaped, film-coated tablets debossed with ‘AN 321’ on one side and plain on the other side.
- 1000 mg light orange to orange colored, capsule shaped, film-coated tablets debossed with ‘AN 323’ on one side and plain on the other side

4 CONTRAINDICATIONS

Niacin extended-release tablets are contraindicated in the following conditions:

- Active liver disease or unexplained persistent elevations in hepatic transaminases [see Warnings and Precautions (5.3)]
- Patients with active peptic ulcer disease
- Patients with arterial bleeding
- Hypersensitivity to niacin or any component of this medication [see Adverse Reactions (6.1)]

5 WARNINGS AND PRECAUTIONS

Niacin extended-release preparations should not be substituted for equivalent doses of immediate-release (crystalline) niacin. For patients switching from immediate-release niacin to niacin extended-release, therapy with niacin extended-release should be initiated with low doses (i.e., 500 mg at bedtime) and the niacin extended-release dose should then be titrated to the desired therapeutic response [see Dosage and Administration (2)] .

Caution should also be used when niacin is used in patients with unstable angina or in the acute phase of an MI, particularly when such patients are also receiving vasoactive drugs such as nitrates, calcium channel blockers, or adrenergic blocking agents.

Niacin is rapidly metabolized by the liver, and excreted through the kidneys. Niacin is contraindicated in patients with significant or unexplained hepatic impairment [see Contraindications (4) and Warnings and Precautions (5.3)] and should be used with caution in patients with renal impairment. Patients with a past history of jaundice, hepatobiliary disease, or peptic ulcer should be observed closely during niacin therapy.

5.1 Mortality and Coronary Heart Disease Morbidity

Niacin extended-release has not been shown to reduce cardiovascular morbidity or mortality among patients already treated with a statin.

The Atherothrombosis Intervention in Metabolic Syndrome with Low HDL/High Triglycerides:

Impact on Global Health Outcomes (AIM-HIGH) trial was a randomized placebo-controlled trial of 3414 patients with stable, previously diagnosed cardiovascular disease. Mean baseline lipid levels were LDL-C 74 mg/dL, HDL-C 35 mg/dL, non-HDL-C 111 mg/dL and median triglyceride level of 163 to 177 mg/dL. Ninety-four percent of patients were on background statin therapy prior to entering the trial. All participants received simvastatin, 40 to 80 mg per day, plus ezetimibe 10 mg per day if needed, to maintain an LDL-C level of 40 to 80 mg/dL, and were randomized to receive niacin extended-release 1500 to 2000 mg/day (n=1718) or matching placebo (IR Niacin, 100 to 150 mg, n=1696). On-treatment lipid changes at two years for LDL-C were -12% for the simvastatin plus niacin extended-release group and -5.5% for the simvastatin plus placebo group. HDL-C increased by 25% to 42 mg/dL in the simvastatin plus niacin extended-release group and by 9.8% to 38 mg/dL in the simvastatin plus placebo group (P<0.001). Triglyceride levels decreased by 28.6% in the simvastatin plus niacin extended-release group and by 8.1% in the simvastatin plus placebo group. The primary outcome was an ITT composite of the first study occurrence of coronary heart disease death, nonfatal myocardial infarction, ischemic stroke, hospitalization for acute coronary syndrome or symptom-driven coronary or cerebral revascularization procedures. The trial was stopped after a mean follow-up period of 3 years owing to a lack of efficacy. The primary outcome occurred in 282 patients in the simvastatin plus niacin extended-release group (16.4%) and in 274 patients in the simvastatin plus placebo group (16.2%) (HR 1.02 [95% CI, 0.87 to 1.21], P=0.79. In an ITT analysis, there were 42 cases of first occurrence of ischemic stroke reported, 27 (1.6%) in the simvastatin plus niacin extended-release group and 15 (0.9%) in the simvastatin plus placebo group, a non-statistically significant result (HR 1.79, [95%CI = 0.95 to 3.36], p=0.071). The on-treatment ischemic stroke events were 19 for the simvastatin plus niacin extended-release group and 15 for the simvastatin plus placebo group [see Adverse Reactions (6.1)] .

5.2 Skeletal Muscle

Cases of rhabdomyolysis have been associated with concomitant administration of lipid-altering doses (≥1 g/day) of niacin and statins. Elderly patients and patients with diabetes, renal failure, or uncontrolled hypothyroidism are particularly at risk. Monitor patients for any signs and symptoms of muscle pain, tenderness, or weakness, particularly during the initial months of therapy and during any periods of upward dosage titration. Periodic serum creatine phosphokinase (CPK) and potassium determinations should be considered in such situations, but there is no assurance that such monitoring will prevent the occurrence of severe myopathy.

5.3 Liver Dysfunction

Cases of severe hepatic toxicity, including fulminant hepatic necrosis, have occurred in patients who have substituted sustained-release (modified-release, timed-release) niacin products for immediate-release (crystalline) niacin at equivalent doses.

Niacin extended-release should be used with caution in patients who consume substantial quantities of alcohol and/or have a past history of liver disease. Active liver diseases or unexplained transaminase elevations are contraindications to the use of niacin extended-release.

Niacin preparations have been associated with abnormal liver tests. In three placebo-controlled clinical trials involving titration to final daily niacin extended-release doses ranging from 500 to 3000 mg, 245 patients received niacin extended-release for a mean duration of 17 weeks. No patient with normal serum transaminase levels (AST, ALT) at baseline experienced elevations to more than 3 times the upper limit of normal (ULN) during treatment with niacin extended-release. In these studies, fewer than 1% (2/245) of niacin extended-release patients discontinued due to transaminase elevations greater than 2 times the ULN.

Liver-related tests should be performed on all patients during therapy with niacin extended-release. Serum transaminase levels, including AST and ALT (SGOT and SGPT), should be monitored before treatment begins, every 6 to 12 weeks for the first year, and periodically thereafter (e.g., at approximately 6-month intervals). Special attention should be paid to patients who develop elevated serum transaminase levels, and in these patients, measurements should be repeated promptly and then performed more frequently. If the transaminase levels show evidence of progression, particularly if they rise to 3 times ULN and are persistent, or if they are associated with symptoms of nausea, fever, and/or malaise, the drug should be discontinued.

5.4 Laboratory Abnormalities

Increase in Blood Glucose: Niacin treatment can increase fasting blood glucose. Frequent monitoring of blood glucose should be performed to ascertain that the drug is producing no adverse effects. Diabetic patients may experience a dose-related increase in glucose intolerance. Diabetic or potentially diabetic patients should be observed closely during treatment with niacin extended-release, particularly during the first few months of use or dose adjustment; adjustment of diet and/or hypoglycemic therapy may be necessary.

Reduction in platelet count: Niacin extended-release has been associated with small but statistically significant dose-related reductions in platelet count (mean of -11% with 2000 mg). Caution should be observed when niacin extended-release is administered concomitantly with anticoagulants; platelet counts should be monitored closely in such patients.

Increase in Prothrombin Time (PT): Niacin extended-release has been associated with small but statistically significant increases in prothrombin time (mean of approximately +4%); accordingly, patients undergoing surgery should be carefully evaluated. Caution should be observed when niacin extended-release is administered concomitantly with anticoagulants; prothrombin time should be monitored closely in such patients.

Increase in Uric Acid: Elevated uric acid levels have occurred with niacin therapy, therefore use with caution in patients predisposed to gout.

Decrease in Phosphorus: In placebo-controlled trials, niacin extended-release has been associated with small but statistically significant, dose-related reductions in phosphorus levels (mean of -13% with 2000 mg). Although these reductions were transient, phosphorus levels should be monitored periodically in patients at risk for hypophosphatemia.

6 ADVERSE REACTIONS

Because clinical studies are conducted under widely varying conditions, adverse reaction rates observed in the clinical studies of a drug cannot be directly compared to rates in the clinical studies of another drug and may not reflect the rates observed in practice.

6.1 Clinical Studies Experience

In the placebo-controlled clinical trials database of 402 patients (age range 21 to 75 years, 33% women, 89% Caucasians, 7% Blacks, 3% Hispanics, 1% Asians) with a median treatment duration of 16 weeks, 16% of patients on niacin extended-release and 4% of patients on placebo discontinued due to adverse reactions. The most common adverse reactions in the group of patients treated with niacin extended-release that led to treatment discontinuation and occurred at a rate greater than placebo were flushing (6% vs. 0%), rash (2% vs. 0%), diarrhea (2% vs. 0%), nausea (1% vs. 0%), and vomiting (1% vs. 0%). The most commonly reported adverse reactions (incidence >5% and greater than placebo) in the niacin extended-release controlled clinical trial database of 402 patients were flushing, diarrhea, nausea, vomiting, increased cough and pruritus.

In the placebo-controlled clinical trials, flushing episodes (i.e., warmth, redness, itching and/or tingling) were the most common treatment-emergent adverse reactions (reported by as many as 88% of patients) for niacin extended-release. Spontaneous reports suggest that flushing may also be accompanied by symptoms of dizziness, tachycardia, palpitations, shortness of breath, sweating, burning sensation/skin burning sensation, chills, and/or edema, which in rare cases may lead to syncope. In pivotal studies, 6% (14/245) of niacin extended-release patients discontinued due to flushing. In comparisons of immediate-release (IR) niacin and niacin extended-release tablets, although the proportion of patients who flushed was similar, fewer flushing episodes were reported by patients who received niacin extended-release. Following 4 weeks of maintenance therapy at daily doses of 1500 mg, the incidence of flushing over the 4-week period averaged 8.6 events per patient for IR niacin versus 1.9 following niacin extended-release.

Other adverse reactions occurring in ≥5% of patients treated with niacin extended-release and at an incidence greater than placebo are shown in Table 2 below.

Table 2. Treatment-Emergent Adverse Reactions by Dose Level in ≥ 5% of Patients and at an Incidence Greater than Placebo; Regardless of Causality Assessment in Placebo-Controlled Clinical Trials

 |  | Placebo-Controlled Studies Niacin Extended-release Treatment@
 |  |  | Recommended Daily Maintenance Doses†
 | Placebo; (n = 157) | 500 mg‡; (n = 87) | 1000 mg; (n = 110) | 1500 mg (n = 136) | 2000 mg; (n = 95)
 | % | % | % | % | %
Gastrointestinal Disorders
Diarrhea | 13 | 7 | 10 | 10 | 14
Nausea | 7 | 5 | 6 | 4 | 11
Vomiting | 4 | 0 | 2 | 4 | 9
Respiratory
Cough, Increased | 6 | 3 | 2 | < 2 | 8
Skin and Subcutaneous Tissue Disorders
Pruritus | 2 | 8 | 0 | 3 | 0
Rash | 0 | 5 | 5 | 5 | 0
Vascular Disorders
Flushing& | 19 | 68 | 69 | 63 | 55
Note: Percentages are calculated from the total number of patients in each column.
† Adverse reactions are reported at the initial dose where they occur.
@ Pooled results from placebo-controlled studies; for niacin extended-release, n = 245 and median treatment duration = 16 weeks. Number of niacin patients (n) are not additive across doses.
‡ The 500 mg/day dose is outside the recommended daily maintenance dosing range [see Dosage and Administration (2)] .
& 10 patients discontinued before receiving 500 mg, therefore they were not included.

In general, the incidence of adverse events was higher in women compared to men.

Atherothrombosis Intervention in Metabolic Syndrome with Low HDL/High Triglycerides:

Impact on Global Health Outcomes (AIM-HIGH)

In AIM-HIGH involving 3414 patients (mean age of 64 years, 15% women, 92% Caucasians, 34% with diabetes mellitus) with stable, previously diagnosed cardiovascular disease, all patients received simvastatin, 40 to 80 mg per day, plus ezetimibe 10 mg per day if needed, to maintain an LDL-C level of 40 to 80 mg/dL, and were randomized to receive niacin extended-release 1500 to 2000 mg/day (n=1718) or matching placebo (IR Niacin, 100 to 150 mg, n=1696). The incidence of the adverse reactions of “blood glucose increased” (6.4% vs. 4.5%) and “diabetes mellitus” (3.6% vs. 2.2%) was significantly higher in the simvastatin plus niacin extended-release group as compared to the simvastatin plus placebo group. There were 5 cases of rhabdomyolysis reported, 4 (0.2%) in the simvastatin plus niacin extended-release group and one (<0.1%) in the simvastatin plus placebo group [see Warnings and Precautions (5.1)] .

6.2 Postmarketing Experience

The following additional adverse reactions have been identified during post-approval use of niacin extended-release. Because the below reactions are reported voluntarily from a population of uncertain size, it is generally not possible to reliably estimate their frequency or establish a causal relationship to drug exposure.
Cardiac disorders: tachycardia, palpitations, atrial fibrillation, other cardiac arrhythmias
Eye disorders: blurred vision, macular edema
Gastrointestinal disorders: peptic ulcers, eructation, flatulence
Hepatobiliary disorders: hepatitis, jaundice
Immune system disorders: hypersensitivity reactions (including anaphylaxis, angioedema, urticaria, flushing, dyspnea, tongue edema, larynx edema, face edema, peripheral edema, laryngismus and vesiculobullous rash)
Metabolism and nutrition disorders: decreased glucose tolerance, gout Musculoskeletal and connective tissue disorders: myalgia, myopathy
Nervous system disorders: dizziness, insomnia, asthenia, nervousness, paresthesia, migraine
Respiratory, thoracic and mediastinal disorders: dyspnea
Skin and subcutaneous tissue disorders: maculopapular rash, dry skin, sweating, burning sensation/skin burning sensation, skin discoloration, acanthosis nigricans
Vascular disorders: syncope, hypotension, postural hypotension

Clinical Laboratory Abnormalities
Chemistry: Elevations in serum transaminases, LDH, fasting glucose, uric acid, total bilirubin, amylase and creatine kinase, and reduction in phosphorus.
Hematology: Slight reductions in platelet counts and prolongation in prothrombin time.

To report SUSPECTED ADVERSE REACTIONS, contact AvKARE at 1-855-361-3993; email drugsafety@avkare.com or FDA at 1-800-FDA-1088 or www.fda.gov/medwatch.

7 DRUG INTERACTIONS

7.1 Statins

Caution should be used when prescribing niacin (≥1 gm/day) with statins as these drugs can increase risk of myopathy/rhabdomyolysis [see Warnings and Precautions (5) and Clinical Pharmacology (12.3)] .

7.2 Bile Acid Sequestrants

An in vitro study results suggest that the bile acid-binding resins have high niacin binding capacity. Therefore, 4 to 6 hours, or as great an interval as possible, should elapse between the ingestion of bile acid-binding resins and the administration of niacin extended-release [see Clinical Pharmacology (12.3)] .

7.3 Aspirin

Concomitant aspirin may decrease the metabolic clearance of nicotinic acid. The clinical relevance of this finding is unclear.

7.4 Antihypertensive Therapy

Niacin may potentiate the effects of ganglionic blocking agents and vasoactive drugs resulting in postural hypotension.

7.5 Other

Vitamins or other nutritional supplements containing large doses of niacin or related compounds such as nicotinamide may potentiate the adverse effects of niacin extended-release.

7.6 Laboratory Test Interactions

Niacin may produce false elevations in some fluorometric determinations of plasma or urinary catecholamines. Niacin may also give false-positive reactions with cupric sulfate solution (Benedict’s reagent) in urine glucose tests.

8 USE IN SPECIFIC POPULATIONS

8.1 Pregnancy

Risk Summary
Discontinue niacin extended-release when pregnancy is recognized in patients receiving the drug for the treatment of hyperlipidemia. Assess the individual risks and benefits of continuing niacin extended-release during pregnancy in patients receiving the drug for the treatment of hypertriglyceridemia. Advise patients to inform their healthcare provider of a known or suspected pregnancy.

The potential for embryofetal toxicity with the doses of niacin in niacin extended-release tablets is unknown. The available data on niacin extended-release use in pregnant women are insufficient to evaluate for a drug-associated risk of major birth defects, miscarriage, or adverse maternal or fetal outcomes. Animal reproduction studies have not been conducted with niacin or with niacin extended-release tablets. Treatment of hypercholesterolemia is not generally necessary during pregnancy. Atherosclerosis is a chronic process and the discontinuation of lipid-lowering drugs during pregnancy should have little impact on the outcome of long-term therapy of primary hypercholesterolemia for most patients.

The estimated background risk of major birth defects and miscarriage for the indicated population is unknown. In the U.S. general population, the estimated background risk of major birth defects and miscarriage in clinically recognized pregnancies is 2% to 4% and 15% to 20%, respectively .

8.2 Lactation

Risk Summary
Niacin is present in human milk and the amount of niacin increases with maternal supplementation. There is no information on the effects of the doses of niacin in niacin extended-release tablets on the breastfed infant or the effects on milk production. Because of the potential for serious adverse reactions in breastfeeding infants, including hepatotoxicity, advise patients not to breastfeed during treatment with niacin extended-release.

8.4 Pediatric Use

Safety and effectiveness of niacin therapy in pediatric patients (≤16 years) have not been established.

8.5 Geriatric Use

Of 979 patients in clinical studies of niacin extended-release, 21% of the patients were age 65 and over. No overall differences in safety and effectiveness were observed between these patients and younger patients, and other reported clinical experience has not identified differences in responses between the elderly and younger patients, but greater sensitivity of some older individuals cannot be ruled out.

8.6 Renal Impairment

No studies have been performed in this population. Niacin extended-release should be used with caution in patients with renal impairment [see Warnings and Precautions (5)] .

8.7 Hepatic Impairment

No studies have been performed in this population. Niacin extended-release should be used with caution in patients with a past history of liver disease and/or who consume substantial quantities of alcohol. Active liver disease, unexplained transaminase elevations and significant or unexplained hepatic dysfunction are contraindications to the use of niacin extended-release [see Contraindications (4.0) and Warnings and Precautions (5.3)] .

8.8 Gender

Data from the clinical trials suggest that women have a greater hypolipidemic response than men at equivalent doses of niacin extended-release.

10 OVERDOSAGE

Supportive measures should be undertaken in the event of an overdose.

11 DESCRIPTION

Niacin extended-release tablets contains niacin, USP, which at therapeutic doses is an antihyperlipidemic agent. Niacin, USP (nicotinic acid, or 3-pyridinecarboxylic acid) is a white, crystalline powder, very soluble in water, with the following structural formula:

Niacin extended-release tablets are unscored, film-coated tablets for oral administration and are available in two tablet strengths containing 500 mg and 1000 mg niacin. The 500 mg is light orange to orange colored, round shaped, coated tablets debossed with ‘AN 321’ on one side and plain on the other side. The 1000 mg is light orange to orange colored, capsule shaped, coated tablets debossed with ‘AN 323’ on one side and plain on the other side. Niacin extended-release tablets also contain the following inactive ingredients: FD&C yellow #6/sunset yellow FCF aluminum lake, hydroxyethyl cellulose, hypromellose, iron oxide red, iron oxide yellow, polyethylene glycol 400, stearic acid and titanium dioxide.

FDA approved dissolution test specifications differ from USP.

12 CLINICAL PHARMACOLOGY

12.1 Mechanism of Action

The mechanism by which niacin alters lipid profiles has not been well defined. It may involve several actions including partial inhibition of release of free fatty acids from adipose tissue, and increased lipoprotein lipase activity, which may increase the rate of chylomicron triglyceride removal from plasma. Niacin decreases the rate of hepatic synthesis of VLDL and LDL, and does not appear to affect fecal excretion of fats, sterols, or bile acids.

12.3 Pharmacokinetics

Absorption

Due to extensive and saturable first-pass metabolism, niacin concentrations in the general circulation are dose dependent and highly variable. Time to reach the maximum niacin plasma concentrations was about 5 hours following niacin extended-release. To reduce the risk of gastrointestinal (GI) upset, administration of niacin extended-release with a low-fat meal or snack is recommended.

Single-dose bioavailability studies have demonstrated that the 500 mg and 1000 mg tablet strengths are dosage form equivalent but the 500 mg and 750 mg tablet strengths are not dosage form equivalent.

Metabolism

The pharmacokinetic profile of niacin is complicated due to extensive first-pass metabolism that is dose-rate specific and, at the doses used to treat dyslipidemia, saturable. In humans, one pathway is through a simple conjugation step with glycine to form nicotinuric acid (NUA). NUA is then excreted in the urine, although there may be a small amount of reversible metabolism back to niacin. The other pathway results in the formation of nicotinamide adenine dinucleotide (NAD). It is unclear whether nicotinamide is formed as a precursor to, or following the synthesis of, NAD. Nicotinamide is further metabolized to at least N-methylnicotinamide (MNA) and nicotinamide-N-oxide (NNO). MNA is further metabolized to two other compounds, N-methyl-2-pyridone-5-carboxamide (2PY) and N-methyl-4-pyridone-5-carboxamide (4PY). The formation of 2PY appears to predominate over 4PY in humans. At the doses used to treat hyperlipidemia, these metabolic pathways are saturable, which explains the nonlinear relationship between niacin dose and plasma concentrations following multiple-dose niacin extended-release administration.

Nicotinamide does not have hypolipidemic activity; the activity of the other metabolites is unknown.

Elimination

Following single and multiple doses, approximately 60% to 76% of the niacin dose administered as niacin extended-release was recovered in urine as niacin and metabolites; up to 12% was recovered as unchanged niacin after multiple dosing. The ratio of metabolites recovered in the urine was dependent on the dose administered.

Pediatric Use

No pharmacokinetic studies have been performed in this population (≤16 years) [see Use in Specific Populations (8.4)] .

Geriatric Use

No pharmacokinetic studies have been performed in this population (> 65 years) [see Use in Specific Populations (8.5)] .

Renal Impairment

No pharmacokinetic studies have been performed in this population. Niacin extended-release should be used with caution in patients with renal disease [see Warnings and Precautions (5)] .

Hepatic Impairment

No pharmacokinetic studies have been performed in this population. Active liver disease, unexplained transaminase elevations and significant or unexplained hepatic dysfunction are contraindications to the use of niacin extended-release [see Contraindications (4) and Warnings and Precautions (5.3)] .

Gender

Steady-state plasma concentrations of niacin and metabolites after administration of niacin extended-release are generally higher in women than in men, with the magnitude of the difference varying with dose and metabolite. This gender differences observed in plasma levels of niacin and its metabolites may be due to gender-specific differences in metabolic rate or volume of distribution. Recovery of niacin and metabolites in urine, however, is generally similar for men and women, indicating that absorption is similar for both genders [see Gender (8.8)] .

Drug interactions

Fluvastatin

Niacin did not affect fluvastatin pharmacokinetics [see Drug Interactions (7.1)] .

Lovastatin

When niacin extended-release 2000 mg and lovastatin 40 mg were co-administered, niacin extended-release increased lovastatin Cmax and AUC by 2% and 14%, respectively, and decreased lovastatin acid Cmax and AUC by 22% and 2%, respectively. Lovastatin reduced niacin extended-release bioavailability by 2% to 3% [see Drug Interactions (7.1)] .

Simvastatin

When niacin extended-release 2000 mg and simvastatin 40 mg were co-administered, niacin extended-release increased simvastatin Cmax and AUC by 1% and 9%, respectively, and simvastatin acid Cmax and AUC by 2% and 18%, respectively. Simvastatin reduced niacin extended-release bioavailability by 2% [see Drug Interactions (7.1)] .

Bile Acid Sequestrants

An in vitro study was carried out investigating the niacin-binding capacity of colestipol and cholestyramine. About 98% of available niacin was bound to colestipol, with 10% to 30% binding to cholestyramine [see Drug Interactions (7.2)] .

13 NONCLINICAL TOXICOLOGY

13.1 Carcinogenesis and Mutagenesis and Impairment of Fertility

Niacin administered to mice for a lifetime as a 1% solution in drinking water was not carcinogenic. The mice in this study received approximately 6 to 8 times a human dose of 3000 mg/day as determined on a mg/m^2 basis. Niacin was negative for mutagenicity in the Ames test. No studies on impairment of fertility have been performed. No studies have been conducted with niacin extended-release regarding carcinogenesis, mutagenesis, or impairment of fertility.

14 CLINICAL STUDIES

14.1 Niacin Clinical Studies

Niacin’s ability to reduce mortality and the risk of definite, nonfatal myocardial infarction (MI) has been assessed in long-term studies. The Coronary Drug Project, completed in 1975, was designed to assess the safety and efficacy of niacin and other lipid-altering drugs in men 30 to 64 years old with a history of MI. Over an observation period of 5 years, niacin treatment was associated with a statistically significant reduction in nonfatal, recurrent MI. The incidence of definite, nonfatal MI was 8.9% for the 1,119 patients randomized to nicotinic acid versus 12.2% for the 2,789 patients who received placebo (p<0.004). Total mortality was similar in the two groups at 5 years (24.4% with nicotinic acid versus 25.4% with placebo; p=N.S.). At the time of a 15-year follow-up, there were 11% (69) fewer deaths in the niacin group compared to the placebo cohort (52% versus 58.2%; p=0.0004). However, mortality at 15 years was not an original endpoint of the Coronary Drug Project. In addition, patients had not received niacin for approximately 9 years, and confounding variables such as concomitant medication use and medical or surgical treatments were not controlled.

The Cholesterol-Lowering Atherosclerosis Study (CLAS) was a randomized, placebo-controlled, angiographic trial testing combined colestipol and niacin therapy in 162 non-smoking males with previous coronary bypass surgery. The primary, per-subject cardiac endpoint was global coronary artery change score. After 2 years, 61% of patients in the placebo cohort showed disease progression by global change score (n=82), compared with only 38.8% of drug-treated subjects (n=80), when both native arteries and grafts were considered (p<0.005); disease regression also occurred more frequently in the drug-treated group (16.2% versus 2.4%; p=0.002). In a follow-up to this trial in a subgroup of 103 patients treated for 4 years, again, significantly fewer patients in the drug-treated group demonstrated progression than in the placebo cohort (48% versus 85%, respectively; p<0.0001).

The Familial Atherosclerosis Treatment Study (FATS) in 146 men ages 62 and younger with Apo B levels ≥125 mg/dL, established coronary artery disease, and family histories of vascular disease, assessed change in severity of disease in the proximal coronary arteries by quantitative arteriography. Patients were given dietary counseling and randomized to treatment with either conventional therapy with double placebo (or placebo plus colestipol if the LDL-C was elevated); lovastatin plus colestipol; or niacin plus colestipol. In the conventional therapy group, 46% of patients had disease progression (and no regression) in at least one of nine proximal coronary segments; regression was the only change in 11%. In contrast, progression (as the only change) was seen in only 25% in the niacin plus colestipol group, while regression was observed in 39%. Though not an original endpoint of the trial, clinical events (death, MI, or revascularization for worsening angina) occurred in 10 of 52 patients who received conventional therapy, compared with 2 of 48 who received niacin plus colestipol.

14.2 Niacin Extended-Release Clinical Studies

Placebo-Controlled Clinical Studies in Patients with Primary Hyperlipidemia and Mixed Dyslipidemia: In two randomized, double-blind, parallel, multi-center, placebo-controlled trials, niacin extended-release dosed at 1000, 1500 or 2000 mg daily at bedtime with a low-fat snack for 16 weeks (including 4 weeks of dose escalation) favorably altered lipid profiles compared to placebo (Table 3). Women appeared to have a greater response than men at each niacin extended-release dose level (see Gender Effect, below).

In a double-blind, multi-center, forced dose-escalation study, monthly 500 mg increases in niacin extended-release dose resulted in incremental reductions of approximately 5% in LDL-C and Apo B levels in the daily dose range of 500 mg through 2000 mg (Table 4). Women again tended to have a greater response to niacin extended-release than men (see Gender Effect, below).

Pooled results for major lipids from these three placebo-controlled studies are shown below (Table 5).

Table 5. Selected Lipid Response to Niacin Extended-Release in Placebo-Controlled Clinical Studies*

 | Mean Baseline and Median Percent Change from Baseline; (25th, 75th Percentiles)
Niacin Extended-Release Dose | n | LDL-C | HDL-C | TG
1000 mg at bedtime | 104
Baseline (mg/dL) |  | 218 | 45 | 172
Percent Change |  | -7 (-15, 0) | +14 (+7, +23) | -16 (-34, +3)
1500 mg at bedtime | 120
Baseline (mg/dL) |  | 212 | 46 | 171
Percent Change |  | -13 (-21, -4) | +19 (+9, +31) | -25 (-45, -2)
2000 mg at bedtime | 85
Baseline (mg/dL) |  | 220 | 44 | 160
Percent Change |  | -16 (-26, -7) | +22 (+15, +34) | -38 (-52, -14)
* Represents pooled analyses of results; minimum duration on therapy at each dose was 4 weeks.

Gender Effect: Combined data from the three placebo-controlled niacin extended-release studies in patients with primary hyperlipidemia and mixed dyslipidemia suggest that, at each niacin extended-release dose level studied, changes in lipid concentrations are greater for women than for men (Table 6).

Table 6. Effect of Gender on Niacin Extended-Release Dose Response

 |  | Mean Percent Change from Baseline
Niacin Extended-Release | N | LDL-C |  | HDL-C |  | TG |  | Apo B
Dose | (M/F) | M | F | M | F | M | F | M | F
500 mg at bedtime | 50/37 | -2 | -5 | +11 | +8 | -3 | -9 | -1 | -5
1000 mg at bedtime | 76/52 | -6* | -11* | +14 | +20 | -10 | -20 | -5* | -10*
1500 mg at bedtime | 104/59 | -12 | -16 | +19 | +24 | -17 | -28 | -13 | -15
2000 mg at bedtime | 75/53 | -15 | -18 | +23 | +26 | -30 | -36 | -16 | -16
n = number of male/female patients enrolled.
* Percent change significantly different between genders (p < 0.05).

Other Patient Populations: In a double-blind, multi-center, 19-week study the lipid-altering effects of niacin extended-release (forced titration to 2000 mg at bedtime) were compared to baseline in patients whose primary lipid abnormality was a low level of HDL-C (HDL-C ≤40 mg/dL, TG ≤400 mg/dL, and LDL-C ≤160, or <130 mg/dL in the presence of CHD). Results are shown below (Table 7).

At niacin extended-release 2000 mg/day, median changes from baseline (25th, 75th percentiles) for LDL-C, HDL-C, and TG were -3% (-14, +12%), +27% (+13, +38%), and -33% (-50, -19%), respectively.

16 HOW SUPPLIED/STORAGE AND HANDLING

Niacin extended-release tablets 500 mg are supplied as light orange to orange colored, round shaped, film-coated tablets debossed with “AN 321” on one side and plain on the other side.

They are available as follows:

NDC 50268-584-13 (10 tablets per card, 3 cards per carton)

Niacin extended-release tablets 1000 mg are supplied as light orange to orange colored, capsule shaped, film-coated tablets debossed with “AN 323” on one side and plain on the other side.

Storage: Store at 20° to 25°C (68° to 77°F) [See USP Controlled Room Temperature].
Dispensed in Blister Punch Material. For Institutional Use Only.

17 PATIENT COUNSELING INFORMATION

17.1 Patient Counseling

Patients should be advised to adhere to their National Cholesterol Education Program (NCEP) recommended diet, a regular exercise program, and periodic testing of a fasting lipid panel.

Patients should be advised to inform other healthcare professionals prescribing a new medication that they are taking niacin extended-release.

The patient should be informed of the following:

Dosing Time

Niacin extended-release tablets should be taken at bedtime, after a low-fat snack. Administration on an empty stomach is not recommended.

Tablet Integrity

Niacin extended-release tablets should not be broken, crushed or chewed, but should be swallowed whole.

Dosing Interruption

If dosing is interrupted for any length of time, their physician should be contacted prior to restarting therapy; re-titration is recommended.

Muscle Pain

Notify their physician of any unexplained muscle pain, tenderness, or weakness promptly. They should discuss all medication, both prescription and over the counter, with their physician.

Flushing

Flushing (warmth, redness, itching and/or tingling of the skin) is a common side effect of niacin therapy that may subside after several weeks of consistent niacin extended-release use. Flushing may vary in severity and is more likely to occur with initiation of therapy, or during dose increases. By dosing at bedtime, flushing will most likely occur during sleep. However, if awakened by flushing at night, the patient should get up slowly, especially if feeling dizzy, feeling faint, or taking blood pressure medications. Advise patients of the symptoms of flushing and how they differ from the symptoms of a myocardial infarction.

Diet

Avoid ingestion of alcohol, hot beverages and spicy foods around the time of taking niacin extended-release to minimize flushing.

Supplements

Notify their physician if they are taking vitamins or other nutritional supplements containing niacin or nicotinamide.

Dizziness

Notify their physician if symptoms of dizziness occur.

Diabetics

If diabetic, to notify their physician of changes in blood glucose.

Pregnancy

Advise patients to inform their healthcare provider of a known or suspected pregnancy to discuss if niacin extended-release should be discontinued [see Use in Specific Populations (8.1)].

Lactation

Advise patients not to breastfeed during treatment with niacin extended-release tablet.

Manufactured For:
AvKARE
Pulaski, TN 38478

Mfg. Rev. 12-2025-06
AV Rev. 02/26(M)

AvPAK

PATIENT INFORMATION

Niacin (NYE-a-sin) Extended-Release Tablets

Read this information carefully before you start taking niacin extended-release tablet(s) and each time you get a refill. There may be new information. This information does not take the place of talking with your doctor about your medical condition or your treatment.

What are niacin extended-release tablet(s)?

Niacin extended-release tablet(s) are a prescription medicine used with diet and exercise to increase the good cholesterol (HDL) and lower the bad cholesterol (LDL) and fats (triglycerides) in your blood.

- Niacin extended-release tablet(s) is also used to lower the risk of heart attack in people who have had a heart attack and have high cholesterol.
- In people with coronary artery disease and high cholesterol, niacin extended-release tablet(s), when used with a bile acid-binding resin (another cholesterol medicine) can slow down or lessen the build-up of plaque (fatty deposits) in your arteries.
- In people with heart problems and well-controlled cholesterol, taking niacin extended-release tablet(s) with another cholesterol-lowering medicine (simvastatin) does not reduce heart attacks or strokes more than taking simvastatin alone.

It is not known if niacin extended-release tablet(s) is safe and effective in children 16 years of age and under.

Who should not take niacin extended-release tablet(s)?

Do not take niacin extended-release tablet(s) if you have:

- liver problems
- a stomach ulcer
- bleeding problems
- an allergy to niacin or any of the ingredients in niacin extended-release tablet(s). See the end of this leaflet for a complete list of ingredients in niacin extended-release tablet(s).

What should I tell my doctor before taking niacin extended-release tablet(s)?

Before you take niacin extended-release tablet(s), tell your doctor, if you:

- have diabetes. Tell your doctor if your blood sugar levels change after you take niacin extended-release tablet(s).
- have gout
- have kidney problems
- are pregnant or plan to become pregnant. It is not known if niacin extended-release tablet(s) will harm your unborn baby. Talk to your doctor if you are pregnant or plan to become pregnant while taking niacin extended-release tablet(s).
- are breast-feeding or plan to breast-feed. Niacin can pass into your breast milk. You and your doctor should decide if you will take niacin extended-release tablet(s) or breast-feed. You should not do both. Talk to your doctor about the best way to feed your baby if you take niacin extended-release tablet(s).

Tell your doctor about all the medicines you take, including prescription and non-prescription medicines, vitamins, herbal supplements or other nutritional supplements containing niacin or nicotinamide. Niacin extended-release tablet(s) and other medicines may affect each other causing side effects. Niacin extended-release tablet(s) may affect the way other medicines work, and other medicines may affect how niacin extended-release tablet(s) works.

Especially tell your doctor if you take:

- other medicines to lower cholesterol or triglycerides
- aspirin
- blood pressure medicines
- blood thinner medicines
- large amounts of alcohol

Know the medicines you take. Keep a list of them to show your doctor and pharmacist when you get a new medicine.

How should I take niacin extended-release tablet(s)?

- Take niacin extended-release tablet(s) exactly as your doctor tells you to take it.
- Take niacin extended-release tablet(s) whole. Do not break, crush or chew niacin extended-release tablet(s) before swallowing.
- Take niacin extended-release tablet(s) 1 time a day at bedtime after a low-fat snack. Niacin extended-release tablet(s) should not be taken on an empty stomach.
- All forms of niacin are not the same as niacin extended-release tablet(s). Do not switch between forms of niacin without first talking to your doctor as severe liver damage can occur.
- Do not change your dose or stop taking niacin extended-release tablet(s) unless your doctor tells you to.
- If you need to stop taking niacin extended-release tablet(s), call your doctor before you start taking niacin extended-release tablet(s) again. Your doctor may need to lower your dose of niacin extended-release tablet(s).
- If you forget to take a dose of niacin extended-release tablet(s), take it as soon as you remember.
- If you take too much niacin extended-release tablet(s), call your doctor right away.
- Medicines used to lower your cholesterol called bile acid resins, such as colestipol and cholestyramine, should not be taken at the same time of day as niacin extended-release tablet(s). You should take niacin extended-release tablet(s) and the bile acid resin medicine at least 4 to 6 hours apart.
- Your doctor may do blood tests before you start taking niacin extended-release tablet(s) and during your treatment. You should see your doctor regularly to check your cholesterol and triglyceride levels and to check for side effects.

What are the possible side effects of niacin extended-release tablet(s)?

Niacin extended-release tablet(s) may cause serious side effects, including:

- severe liver problems. Signs of liver problems include:
  - increased tiredness
  - dark colored urine (tea-colored)
  - loss of appetite
  - light colored stools
  - nausea
  - right upper stomach (abdomen) pain
  - yellowing of your skin or whites of your eye
  - itchy skin

- unexplained muscle pain, tenderness or weakness
- high blood sugar level (glucose)
  Call your doctor right away if you have any of the side effects listed above.
  The most common side effects of niacin extended-release tablet(s) include:
- flushing
- diarrhea
- nausea
- vomiting
- increased cough
- rash

Flushing is the most common side effect of niacin extended-release tablet(s). Flushing happens when tiny blood vessels near the surface of the skin (especially on the face, neck, chest and/or back) open wider. Symptoms of flushing may include any or all of the following:

- warmth
- redness
- itching
- tingling of the skin

Flushing does not always happen. If it does, it is usually within 2 to 4 hours after taking a dose of niacin extended-release tablet(s). Flushing may last for a few hours. Flushing is more likely to happen when you first start taking niacin extended-release tablet(s) or when your dose of niacin extended-release tablet(s) is increased. Flushing may get better after several weeks.

If you wake up at night because of flushing, get up slowly, especially if you:

- feel dizzy or faint
- take blood pressure medicines

To lower your chance of flushing:

- Ask your doctor if you can take aspirin to help lower the flushing side effect from niacin extended-release tablets. You can take aspirin (up to the recommended dose of 325 mg) about 30 minutes before you take niacin extended-release tablets to help lower the flushing side effect.
- Do not drink hot beverages (including coffee), alcohol, or eat spicy foods around the time you take niacin extended-release tablet(s).
- Take niacin extended-release tablet(s) with a low-fat snack to lessen upset stomach.

People with high cholesterol and heart disease are at risk for a heart attack. Symptoms of a heart attack may be different from a flushing reaction from niacin extended-release tablet(s). The following may be symptoms of a heart attack due to heart disease and not a flushing reaction:

- chest pain
- pain in other areas of your upper body such as one or both arms, back, neck, jaw or stomach
- shortness of breath
- sweating
- nausea
- lightheadedness

The chest pain you have with a heart attack may feel like uncomfortable pressure, squeezing, fullness or pain that lasts more than a few minutes, or that goes away and comes back. Heart attacks may be sudden and intense, but often start slowly, with mild pain or discomfort.

Call your doctor right away if you have any symptoms of a heart attack.

Tell your doctor if you have any side effect that bothers you or does not go away.

These are not all the possible side effects of niacin extended-release tablet(s). For more information, ask your doctor or pharmacist.

Call your doctor for medical advice about side effects. You may report side effects to FDA at 1-800-FDA-1088.

How should I store niacin extended-release tablet(s)?

- Store niacin extended-release tablets at 68ºF to 77ºF (20ºC to 25ºC).

Keep niacin extended-release tablet(s) and all medicines out of the reach of children.

General information about the safe and effective use of niacin extended-release tablet(s).

Medicines are sometimes prescribed for purposes other than those listed in a Patient Information leaflet. Do not use niacin extended-release tablet(s) for a condition for which it was not prescribed. Do not give niacin extended-release tablet(s) to other people, even if they have the same symptoms that you have. It may harm them.

This Patient Information leaflet summarizes the most important information about niacin extended-release tablet(s). If you would like more information, talk with your doctor. You can ask your pharmacist or doctor for information about niacin extended-release tablet(s) that is written for health professionals.

For more information, go to www.avkare.com or call AvKARE at 1-855-361-3993.

What are the ingredients in niacin extended-release tablet(s)?

Active ingredient:

Niacin, USP

Inactive Ingredients:

FD&C yellow #6/sunset yellow FCF aluminum lake, hydroxyethyl cellulose, hypromellose, iron oxide red, iron oxide yellow, polyethylene glycol 400, stearic acid and titanium dioxide

This Patient Information has been approved by the U.S. Food and Drug Administration.

Manufactured For:
AvKARE
Pulaski, TN 38478

Mfg. Rev. 12-2025-06
AV Rev. 02/26(M)

AvPAK

Dispense with Patient Information available at: www.avkare.com